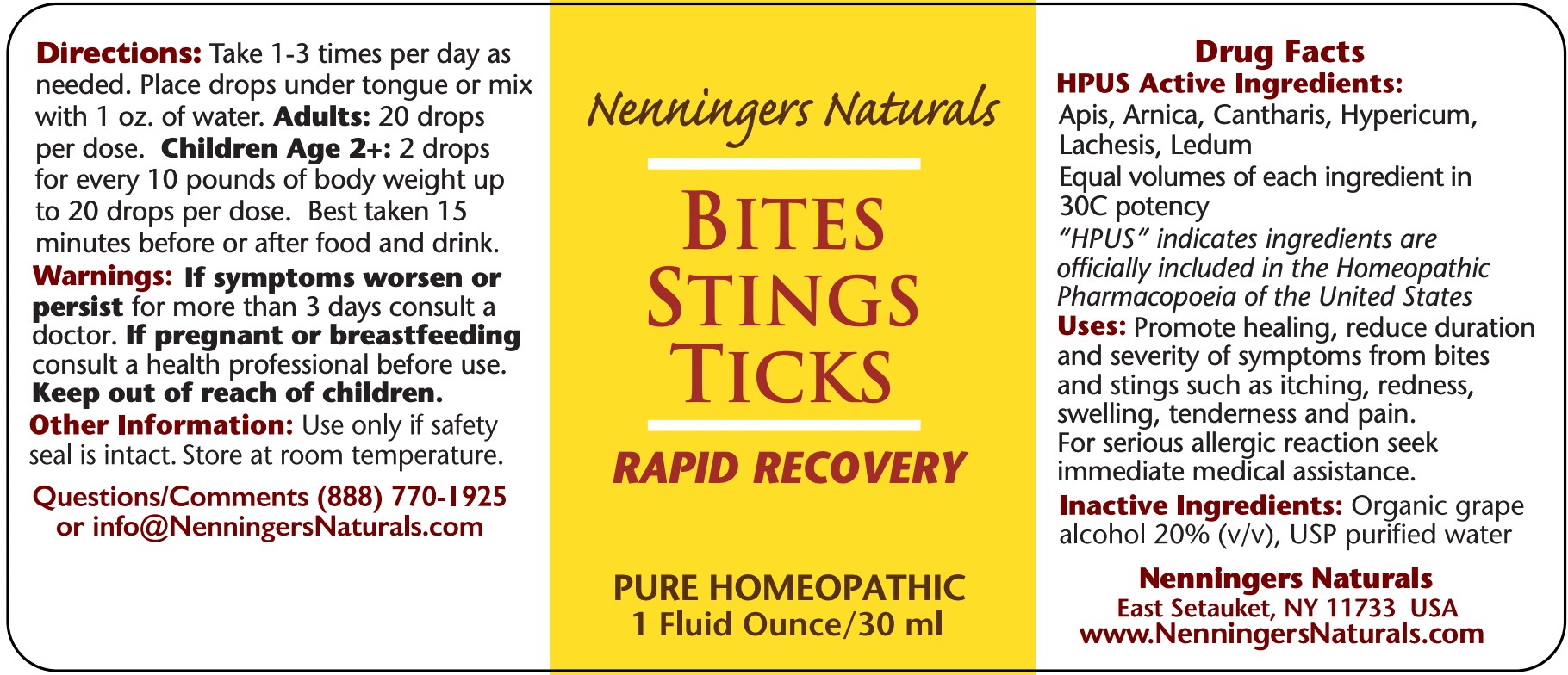 DRUG LABEL: Nenningers Naturals
NDC: 42731-075 | Form: LIQUID
Manufacturer: Nenningers Naturals, LLC
Category: homeopathic | Type: HUMAN OTC DRUG LABEL
Date: 20251225

ACTIVE INGREDIENTS: LACHESIS MUTA VENOM 30 [hp_C]/30 mL; LYTTA VESICATORIA 30 [hp_C]/30 mL; ARNICA MONTANA 30 [hp_C]/30 mL; APIS MELLIFERA 30 [hp_C]/30 mL; ST. JOHN'S WORT 30 [hp_C]/30 mL; LEDUM PALUSTRE TWIG 30 [hp_C]/30 mL
INACTIVE INGREDIENTS: ALCOHOL; WATER

Bites Stings Ticks

ACTIVE INGREDIENT

Active Ingredients: Apis, Arnica, Cantharis, Hypericum, Lachesis, Ledum. All HPUS.

Purpose: Homeopathic medicine for symptom relief from bites and stings.

PURPOSE

Homeopathic medicine for symptom relief from bites and stings.

INACTIVE INGREDIENT

Alcohol, USP purified Water

Uses:

Promote healing, reduce duration and severity of symptoms from bites and stings such as itching, redness, swelling, tenderness and pain. For serious allergic reactions seek immediate medical assistance.

Warnings:

If symptoms worsen or persist for more than 3 days consult a physician.

If pregnant or breastfeeding consult a physician before use.

Keep out of reach of children.

Keep out of reach of children

Directions:

Take 1 to 3 times per day as needed. Place drops under the tongue or mix with 1 oz. of water. Adults: 20 drops
per dose. Children Aged 2+: 2 drops

for every 10 pounds of body weight, up to 20 drops per dose. Best taken 15 minutes before or after food and drink.

Other information:

Use only if the safety seal is intact. Store at room temperature and away from direct sunlight.

Package: 30mL NDC: 42731-075-01